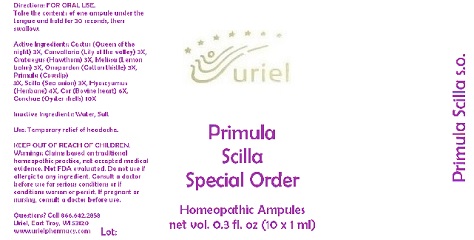 DRUG LABEL: Primula Scilla Special Order
NDC: 48951-8067 | Form: LIQUID
Manufacturer: Uriel Pharmacy Inc.
Category: homeopathic | Type: HUMAN OTC DRUG LABEL
Date: 20170803

ACTIVE INGREDIENTS: SELENICEREUS GRANDIFLORUS STEM 3 [hp_X]/1 mL; CONVALLARIA MAJALIS 3 [hp_X]/1 mL; HAWTHORN LEAF WITH FLOWER 3 [hp_X]/1 mL; MELISSA OFFICINALIS 3 [hp_X]/1 mL; ONOPORDUM ACANTHIUM FLOWER 3 [hp_X]/1 mL; PRIMULA VERIS FLOWER 3 [hp_X]/1 mL; DRIMIA MARITIMA BULB 3 [hp_X]/1 mL; HYOSCYAMUS NIGER LEAF 4 [hp_X]/1 mL; BEEF HEART 6 [hp_X]/1 mL; OSTREA EDULIS SHELL 10 [hp_X]/1 mL
INACTIVE INGREDIENTS: WATER; SODIUM CHLORIDE

Primula Scilla Special Order

INDICATIONS AND USAGE

Directions: FOR ORAL USE.

DOSAGE AND ADMINISTRATION

Take the contents of one ampule under the tongue and hold for 30 seconds, then swallow.

ACTIVE INGREDIENT

Active Ingredients: Cactus (Queen of the night) 3X, Convallaria (Lily of the valley) 3X, Crataegus (Hawthorn) 3X, Melissa (Lemon balm) 3X, Onopordon (Cotton thistle) 3X, Primula (Cowslip)
3X, Scilla (Sea onion) 3X, Hyoscyamus (Henbane) 4X, Cor (Bovine heart) 6X, Conchae (Oyster shells) 10X

Inactive Ingredients: Water, Salt

PURPOSE

Use: Temporary relief of headache.

KEEP OUT OF REACH OF CHILDREN.

WARNINGS

Warnings: Claims based on traditional homeopathic practice, not accepted medical evidence. Not FDA evaluated. Do not use if allergic to any ingredient. Consult a doctor before use for serious conditions or if conditions worsen or persist. If pregnant or nursing, consult a doctor before use.

QUESTIONS

Questions? Call 866.642.2858 Uriel, East Troy, WI 53120 www.urielpharmacy.com